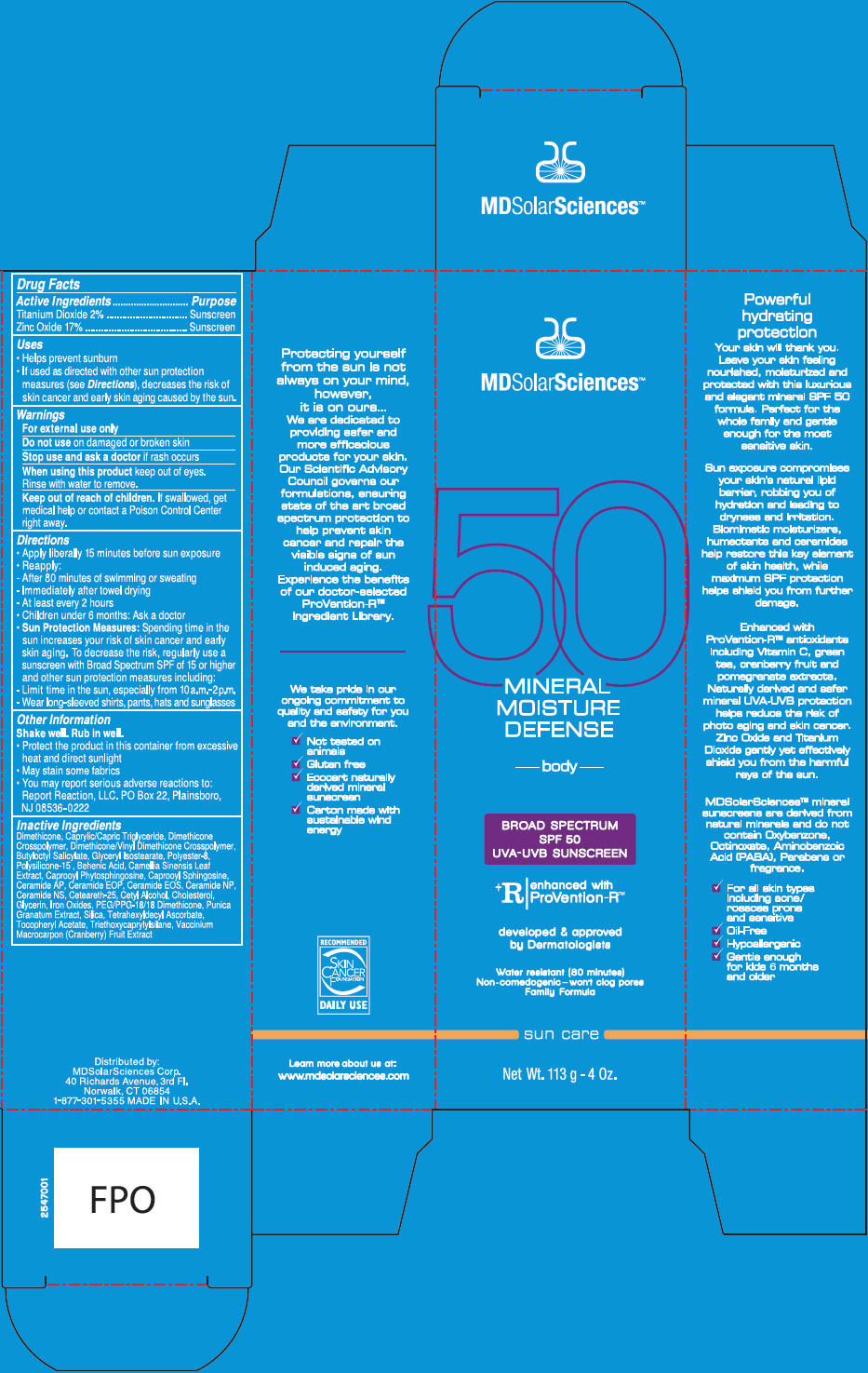 DRUG LABEL: Mineral Moisture Defense 
NDC: 49358-558 | Form: CREAM
Manufacturer: MDSolarSciences
Category: otc | Type: HUMAN OTC DRUG LABEL
Date: 20181108

ACTIVE INGREDIENTS: TITANIUM DIOXIDE 2.7 g/35 g; ZINC OXIDE 1.3 g/35 g
INACTIVE INGREDIENTS: DIMETHICONE; MEDIUM-CHAIN TRIGLYCERIDES; DIMETHICONE/DIENE DIMETHICONE CROSSPOLYMER; DIMETHICONE/VINYL DIMETHICONE CROSSPOLYMER (SOFT PARTICLE); BUTYLOCTYL SALICYLATE; GLYCERYL ISOSTEARATE; POLYESTER-8 (1400 MW, CYANODIPHENYLPROPENOYL CAPPED); POLYSILICONE-15; BEHENIC ACID; GREEN TEA LEAF; CAPROOYL TETRAPEPTIDE-3; N-HEXANOYLSPHINGOSINE; CERAMIDE AP; CERAMIDE 9; 3-DEHYDROXY CERAMIDE 1; CERAMIDE NP; CERAMIDE NG; CETYL ALCOHOL; CHOLESTEROL; GLYCERIN; FERRIC OXIDE RED; PEG/PPG-18/18 DIMETHICONE; POMEGRANATE JUICE; SILICON DIOXIDE; TETRAHEXYLDECYL ASCORBATE; .ALPHA.-TOCOPHEROL ACETATE; TRIETHOXYCAPRYLYLSILANE; CRANBERRY

Mineral Moisture Defense
Broad Spectrum SPF 50 Sunscreen UVA-UVB Suncreen

Drug Facts

ACTIVE INGREDIENT

Active Ingredients | Purpose
Titanium Dioxide 2% | Sunscreen
Zinc Oxide 17% | Sunscreen

Uses

- Helps prevent sunburn
- If used with other sun protection measures (see Directions), decreases the risk of skin cancer and early skin aging caused by the sun.

Warnings

For external use only

Do not use on damaged or broken skin

Stop use and ask a doctor if rash occurs

When using this product keep out of eyes. Rinse with water to remove.

Keep out of reach of children. If swallowed, get medical help or contact a Poison Control Center right away.

Directions

- Apply liberally 15 minutes before sun exposure
- Reapply:
  - After 80 minutes of swimming or sweating
  - Immediately after towel drying
  - At least every 2 hours
  - Children under 6 months: Ask a doctor
- Sun Protection Measures: Spending time in the sun increases your risk of skin cancer and early skin aging. To decrease the risk, regularly use a sunscreen with Broad Spectrum SPF of 15 or higher and other sun protection measures including:
  - Limit time in the sun, especially from 10a.m. – 2p.m.
  - Wear long-sleeved shirts, pants, hats and sunglasses

Other Information

Shake well. Rub in well.

- Protect the product in this container from excessive heat and direct sunlight
- May stain some fabrics
- You may report serious adverse reactions to:
  Report Reaction, LLC. PO Box 22, Plainsboro, NJ 08536-0222

Inactives

Dimethicone, Caprylic/Capric Triglyceride, Dimethicone Crosspolymer, Dimethicone/Vinyl Dimethicone Crosspolymer, Butyloctyl Salicylate, Glyceryl Isostearate, Polyester-8, Polysilicone-15, Behenic Acid, Camelia Sinensis Leaf Extract, Caprooyl Phytosphingosine, Ceramide AP, Ceramide EOP, Ceramide EOS, Ceramide NP, Ceramide NS, Ceteareth-25, Cetyl Alcohol, Cholesterol, Glycerin, Iron Oxides, PEG/PPG-18/18 Dimethicone, Punica Granatum Extract, Silica, Tetrahexyldecyl Ascorbate, Tocopheryl Acetate, Triethoxycaprylysilane, Vaccinum Macrocarpon (Cranberry) Fruit Extract

Distributed by:
MDSolarSciences Corp.
40 Richards Avenue, 3rd Fl., Norwalk, CT 06854

PRINCIPAL DISPLAY PANEL - 113 g Tube Carton

MDSolarSciences™

50
MINERAL
MOISTURE
DEFENSE

body

BROAD SPECTRUM
SPF 50
UVA-UVB SUNSCREEN

^+R
enhanced with
ProVention-R™

developed & approved
by Dermatologists

Water resistant (80 minutes)
Non-comedogenic – won't clog pores
Family Formula

sun care

Net Wt. 113 g - 4 Oz.